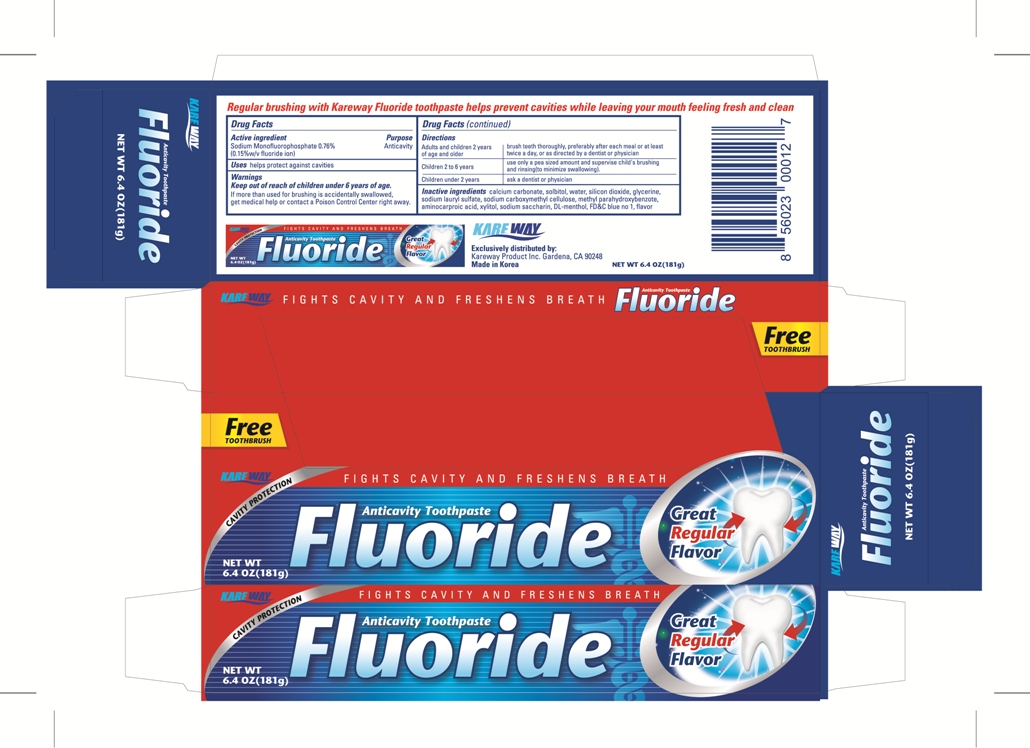 DRUG LABEL: Regular
NDC: 67510-0012 | Form: PASTE, DENTIFRICE
Manufacturer: Kareway Product, Inc.
Category: otc | Type: HUMAN OTC DRUG LABEL
Date: 20120202

ACTIVE INGREDIENTS: SODIUM MONOFLUOROPHOSPHATE 0.76 g/100 g
INACTIVE INGREDIENTS: CALCIUM CARBONATE; SORBITOL; WATER; SILICON DIOXIDE; GLYCERIN; SODIUM LAURYL SULFATE; CARBOXYMETHYLCELLULOSE SODIUM; METHYLPARABEN; AMINOCAPROIC ACID; XYLITOL; SACCHARIN SODIUM; MENTHOL; FD&C BLUE NO. 1

Drug Facts

Active ingredient

Sodium Monofluorophosphate 0.76% (0.15%w/v fluoride ion)

Purpose

Anticavity

Usage

helps protect against cavities

Warnings

Enter section text here

Keep out of reach of children under 6 years of age.

If more than used for brushing is accidentally swallowed, get medical help or contact a Poison Control Center right away.

Directions

Adults and children 2 years of age and older | brush teeth thoroughly, preferably after each meal or at least twice a day, or as directed by a dentist or physician
Children 2 to 6 years | use only a pea sized amount and supervise child's brushing and rinsing (to minimize swallowing).
Children under 2 years | ask a dentist or physician

Inactive ingredients

calcium carbonate, sorbitol, water, silicon dioxide, glycerine, sodium lauryl sulfate, sodium carboxymethyl cellulose, methyl parahydroxybenzoate, aminocaproic acid, xylitol, sodium saccharin, DL-menthol, flavor

PACKAGE LABEL

Enter section text here